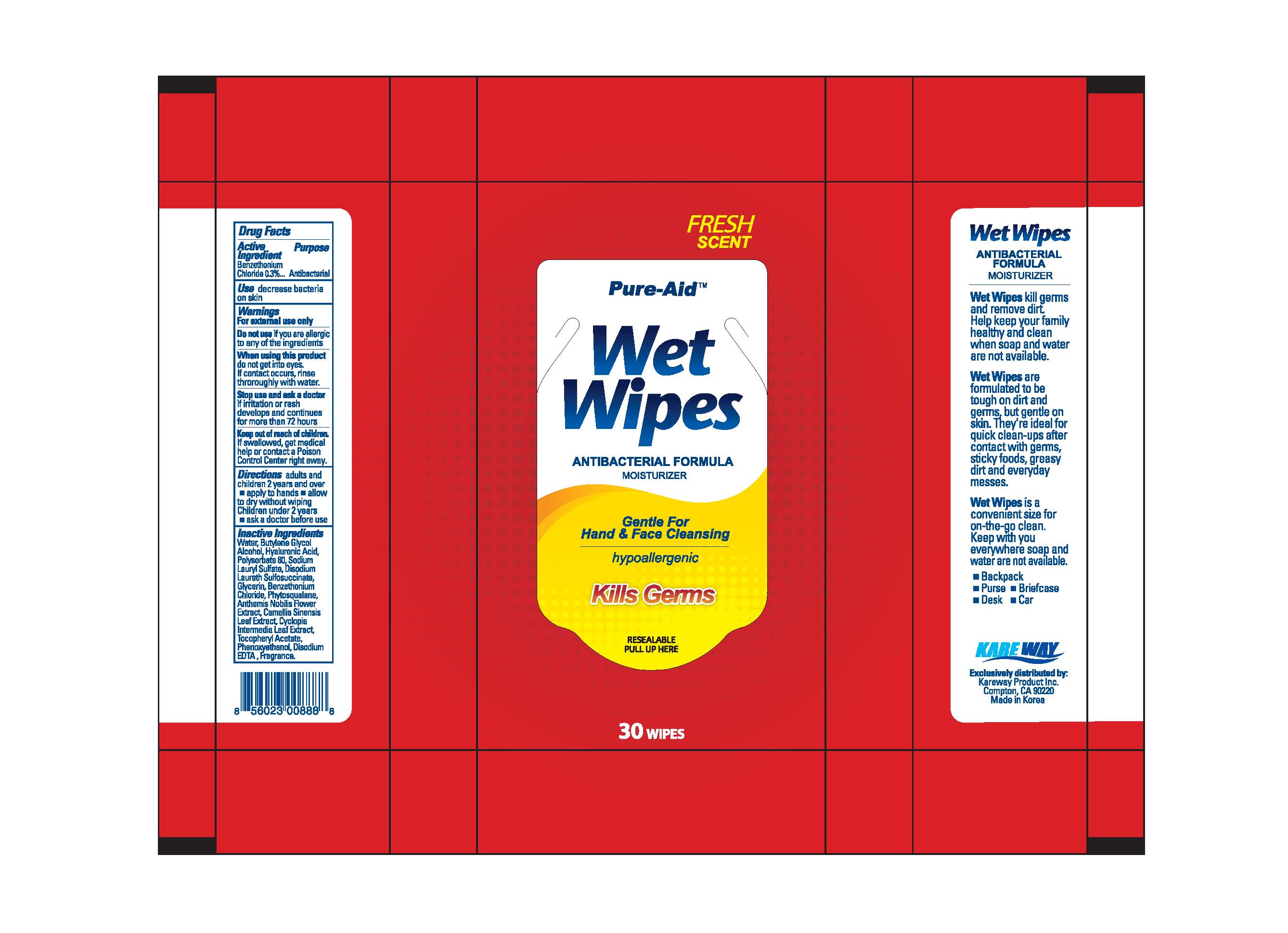 DRUG LABEL: Wet Wipes
NDC: 67510-0888 | Form: SWAB
Manufacturer: Kareway Product, Inc.
Category: otc | Type: HUMAN OTC DRUG LABEL
Date: 20200729

ACTIVE INGREDIENTS: BENZETHONIUM CHLORIDE 0.3 1/100 1
INACTIVE INGREDIENTS: WATER; ALCOHOL; BUTYLENE GLYCOL; HYALURONIC ACID; POLYSORBATE 80; SODIUM LAURYL SULFATE; EDETATE DISODIUM; DISODIUM LAURETH SULFOSUCCINATE; GLYCERIN; CYCLOPIA INTERMEDIA LEAF; PHENOXYETHANOL

Pure-Aid Wet Wipes

Active Ingredients

Benzethonium Chloride 0.3%

Purpose

Antibacterial

Use

decrease bacteria on skin

Warnings

For external use only

Do not use

if you are allergic to any of the ingredients

When using this product

do not get into eyes. If contact occurs, rinse throroughly with water.

Stop use and ask a doctor

if irritation or rash develops and continues for more than 72 hours

Keep out of reach of children

If swallowed, get medical help or contact a Poison Control Center right away.

Directions

adults and children 2 years and over

- apply to hands
- allow to dry without wiping

Children under 2 years

- ask a doctor before use

Inactive Ingredients

Water, Butylene Glycol, Alcohol, Hyaluronic Acid, Polysorbate 80, Sodium Lauryl Sulfate, Disodium Lareth Sulfosuccinate,

Glycerin, Phytosqualane, Anthemis Nobilis Flower Extract, Camellia Sinensis Leaf Extract, Cyclopia Intermedia Leaf Extract,

Tocopheryl Acetate, Phenoxyethanol, Disodium EDTA, Fragrance

Principle Display Panel

Fresh Scent

Wet wiptes

Antibacterial formula

30 wipes